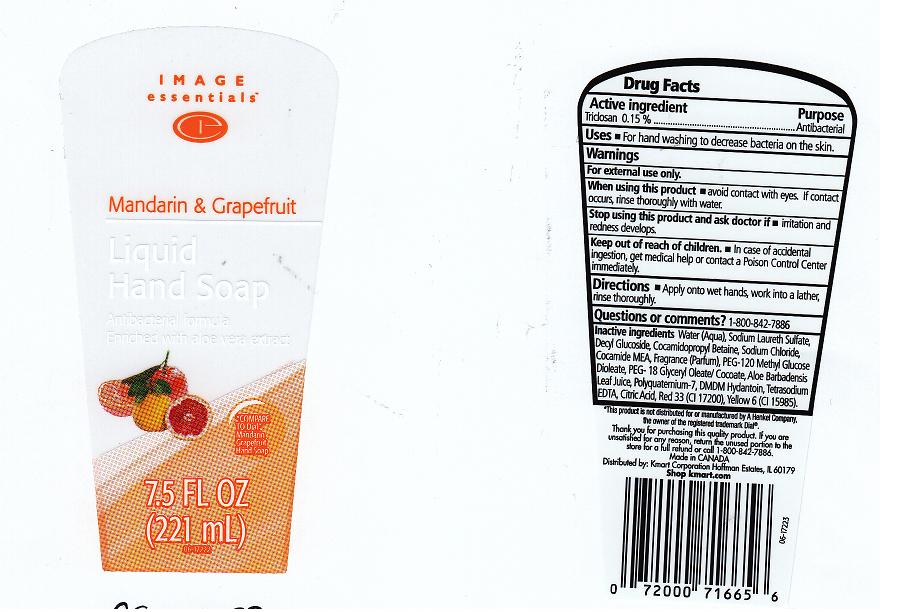 DRUG LABEL: ANTIBACTERIAL
NDC: 49738-215 | Form: LIQUID
Manufacturer: KMART CORPORATION
Category: otc | Type: HUMAN OTC DRUG LABEL
Date: 20110707

ACTIVE INGREDIENTS: TRICLOSAN 0.15 mL/100 mL
INACTIVE INGREDIENTS: WATER; SODIUM LAURETH SULFATE; DECYL GLUCOSIDE; COCAMIDOPROPYL BETAINE; SODIUM CHLORIDE; COCO MONOETHANOLAMIDE; PEG-120 METHYL GLUCOSE DIOLEATE; 1-GLYCERYL MONOOLEATE; ALOE VERA LEAF; POLYQUATERNIUM-7 (70/30 ACRYLAMIDE/DADMAC; 1600 KD); DMDM HYDANTOIN; EDETATE SODIUM; CITRIC ACID MONOHYDRATE; D&C RED NO. 33; FD&C YELLOW NO. 6

DRUG FACTS

ACTIVE INGREDIENT

TRICLOSAN 0.15%

PURPOSE

ANTIBACTERIAL

USES

FOR HAND WASHING TO DECREASE BACTERIA ON THE SKIN.

WARNINGS

FOR EXTERNAL USE ONLY.

WHEN USING THIS PRODUCT

AVOID CONTACT WITH EYES. IF CONTACT OCCURS, RINSE THROUGHLY WITH WATER.

STOP USING THIS PRODUCT AND ASK DOCTOR IF

IRRITATION AND REDNESS DEVELOP.

KEEP OUT OF REACH OF CHILDREN

IN CASE OF ACCIDENTAL INGESTION, GET MEDICAL HELP OR CONTACT A POISON CONTROL CENTER IMMEDIATELY.

DIRECTIONS

APPLY ONTO WET HANDS, WORK INTO A LATHER, RINSE THOROUGHLY.

QUESTIONS OR COMMENTS

1-800-842-7886

INACTIVE INGREDIENTS

Water (Aqua), Sodium Laureth Sulfate, Decyl Glucoside, Cocamidopropyl Betaine, Sodium Chloride, Cocamide MEA, Fragrance (Parfum), PEG-120 Methyl Glucose Dioleate, PEG- 18 Glyceryl Oleate/Cocoate, Aloe Barbadensis Leaf Juice, Polyquaternium-7, DMDM Hydantoin, Tetrasodium EDTA, Citric Acid, Red 33 (CI 17200), Yellow 6 (CI 15985).